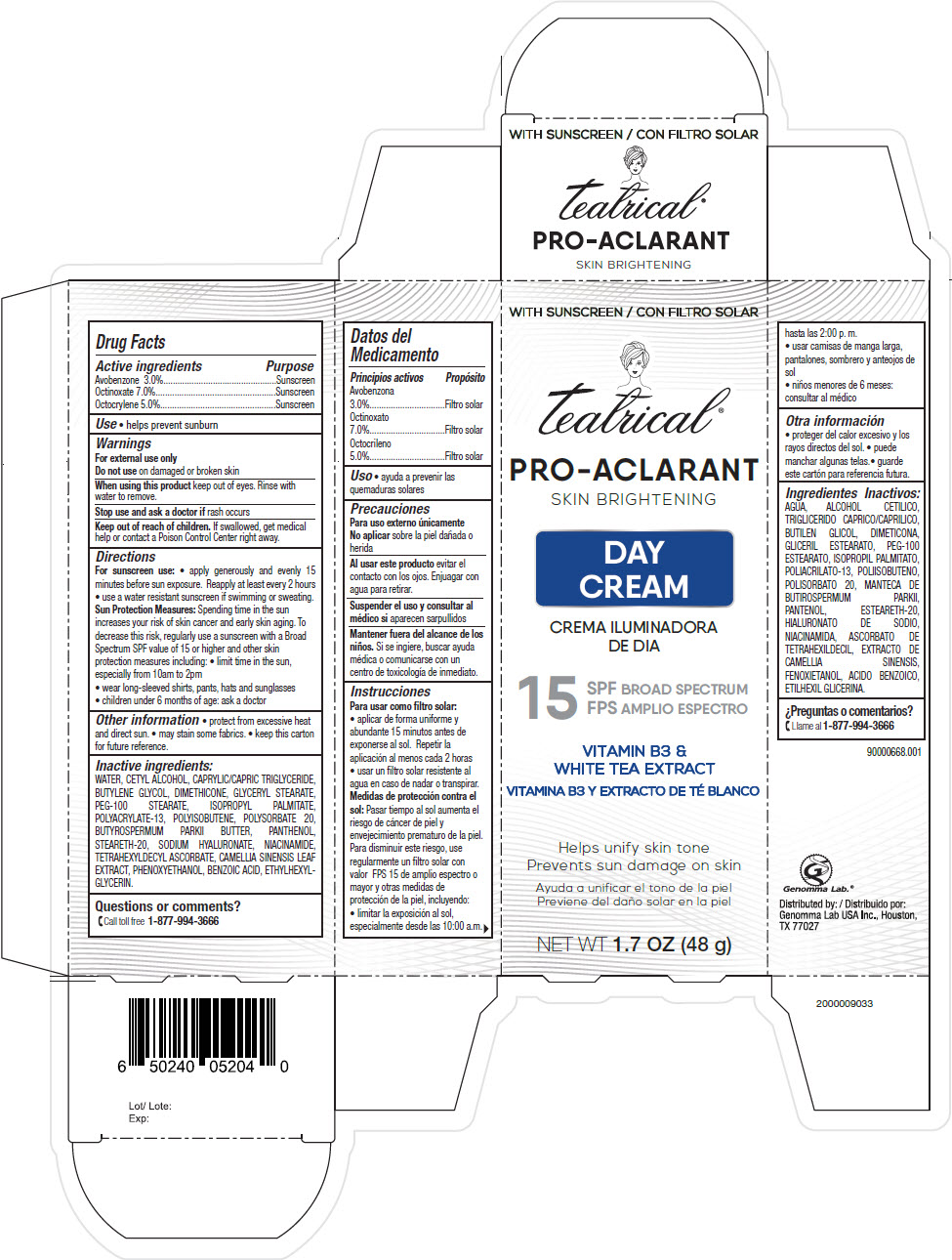 DRUG LABEL: Teatrical Pro-Aclarant Day
NDC: 50066-071 | Form: CREAM
Manufacturer: Genomma Lab USA
Category: otc | Type: HUMAN OTC DRUG LABEL
Date: 20200422

ACTIVE INGREDIENTS: Avobenzone 30 mg/1 g; Octinoxate 70 mg/1 g; Octocrylene 50 mg/1 g
INACTIVE INGREDIENTS: GLYCERYL MONOSTEARATE; Cetyl alcohol; PEG-100 stearate; MEDIUM-CHAIN TRIGLYCERIDES; Butylene Glycol; Dimethicone

Teatrical® Pro-Aclarant Day Cream

Drug Facts

ACTIVE INGREDIENT

Active ingredients | Purpose
Avobenzone 3.0% | Sunscreen
Octinoxate 7.0% | Sunscreen
Octocrylene 5.0% | Sunscreen

Use

- helps prevent sunburn

Warnings

For external use only

Do not use on damaged or broken skin

When using this product keep out of eyes. Rinse with water to remove.

Stop use and ask a doctor if rash occurs

Keep out of reach of children. If swallowed, get medical help or contact a Poison Control Center right away.

Directions

For sunscreen use

- apply generously and evenly 15 minutes before sun exposure. Reapply at least every 2 hours
- use a water resistant sunscreen if swimming or sweating.

Sun Protection Measures

Spending time in the sun increases your risk of skin cancer and early skin aging. To decrease this risk, regularly use a sunscreen with a Broad Spectrum SPF value of 15 or higher and other skin protection measures including:

- limit time in the sun, especially from 10am to 2pm
- wear long-sleeved shirts, pants, hats and sunglasses
- children under 6 months of age: ask a doctor

Other information

- protect from excessive heat and direct sun.
- may stain some fabrics.
- keep this carton for future reference.

Inactive ingredients

WATER, CETYL ALCOHOL, CAPRYLIC/CAPRIC TRIGLYCERIDE, BUTYLENE GLYCOL, DIMETHICONE, GLYCERYL STEARATE, PEG-100 STEARATE, ISOPROPYL PALMITATE, POLYACRYLATE-13, POLYISOBUTENE, POLYSORBATE 20, BUTYROSPERMUM PARKII BUTTER, PANTHENOL, STEARETH-20, SODIUM HYALURONATE, NIACINAMIDE, TETRAHEXYLDECYL ASCORBATE, CAMELLIA SINENSIS LEAF EXTRACT, PHENOXYETHANOL, BENZOIC ACID, ETHYLHEXYLGLYCERIN.

Questions or comments?

Call toll free 1-877-994-3666

Distributed by:
Genomma Lab USA Inc., Houston,
TX 77027

PRINCIPAL DISPLAY PANEL - 48 g Tube Carton

WITH SUNSCREEN

teatrical®

PRO-ACLARANT
SKIN BRIGHTENING

DAY
CREAM

15
SPF BROAD SPECTRUM

VITAMIN B3 &
WHITE TEA EXTRACT

Helps unify skin tone
Prevents sun damage on skin

NET WT 1.7 OZ (48 g)